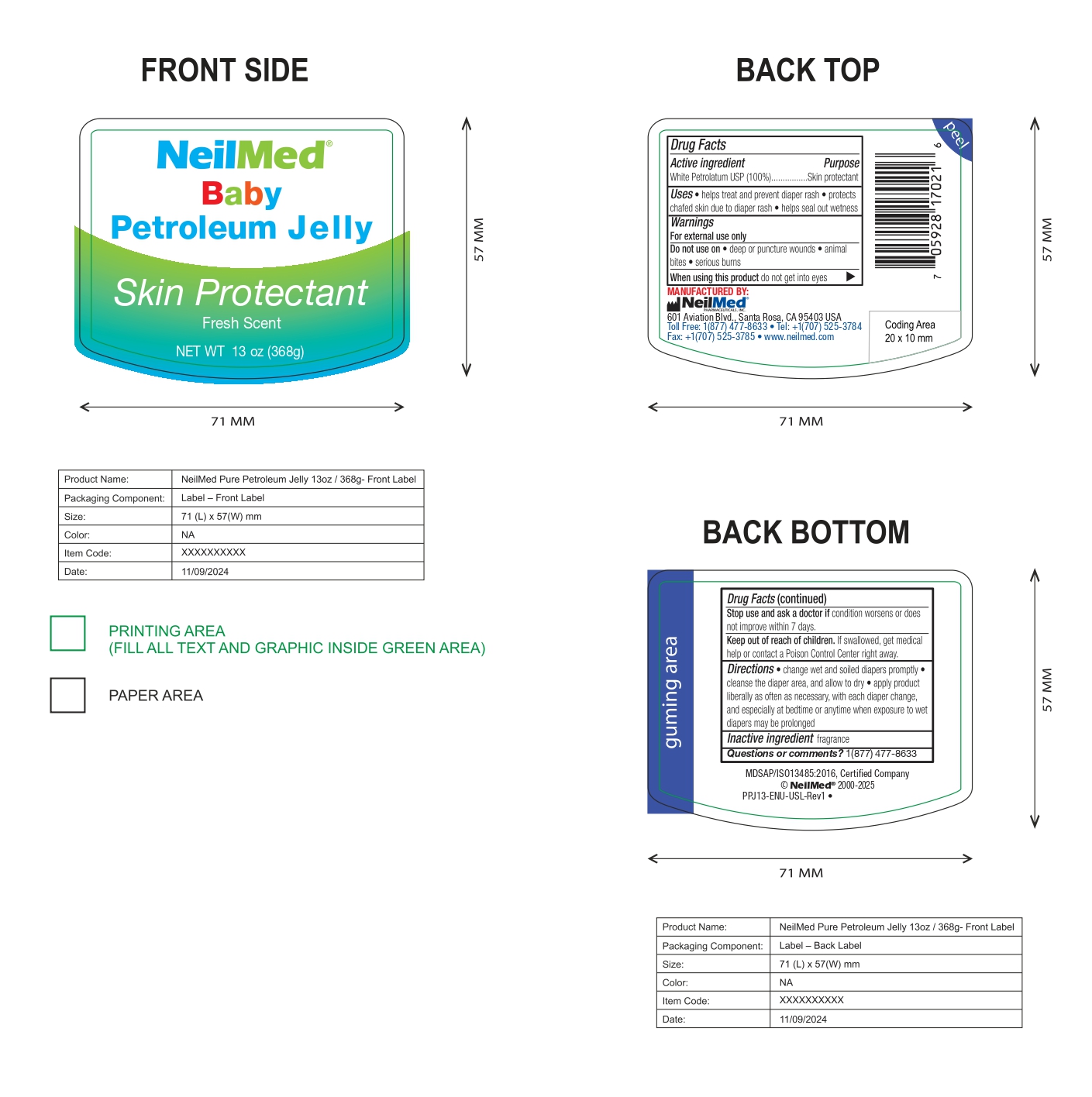 DRUG LABEL: Petroleum Jelly
NDC: 13709-337 | Form: JELLY
Manufacturer: NeilMed Pharmaceuticals Inc.
Category: otc | Type: HUMAN OTC DRUG LABEL
Date: 20250804

ACTIVE INGREDIENTS: WHITE PETROLATUM 100 g/100 g

Baby Petroleum Jelly

Active Ingredient

White Petrolatum USP (100%)

Purpose

White Petrolatum USP (100%).......Skin protectant

Uses

- helps treat and prevent diaper rash
- protects chafed skin due to diaper rash
- helps seal out wetness

Warnings

For external use only

Do not use on

- deep or puncture wounds
- animal bites
- serious burns

When using this product

do not get into eyes

Stop use and ask a doctor if

condition worsens or does not improve within 7 days.

Keep out of reach of children.

If swallowed, get medical help or contact a Poison Control Center right away.

Directions

- change wet and soiled diapers promptly
- cleanse the diaper area, and allow to dry
- apply product liberally as often as necessary, with each diaper change, and especially at bedtime or anytime when exposure to wet diapers may be prolonged

Inactive Ingredient

Fragrance

Questions or comments?

1(877)477-8633